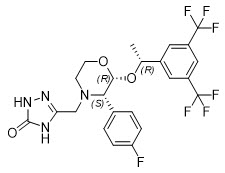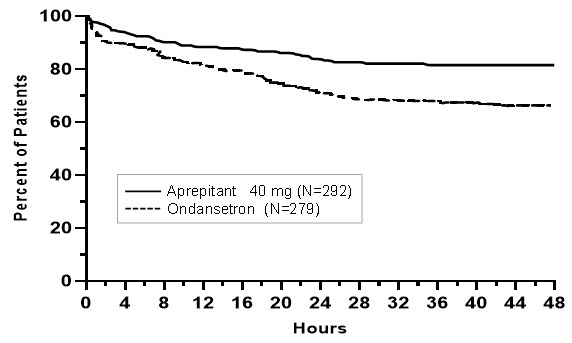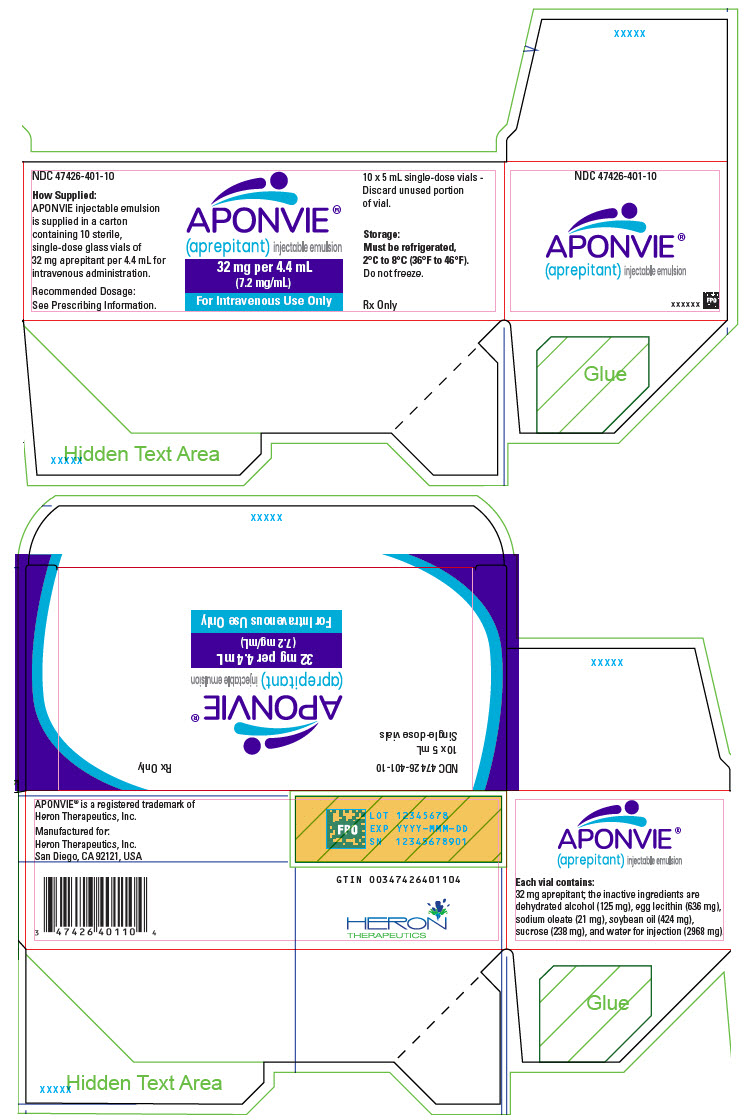 DRUG LABEL: APONVIE
NDC: 47426-401 | Form: EMULSION
Manufacturer: Heron Therapeutics, Inc.
Category: prescription | Type: HUMAN PRESCRIPTION DRUG LABEL
Date: 20251121

ACTIVE INGREDIENTS: APREPITANT 32 mg/4.4 mL
INACTIVE INGREDIENTS: EGG PHOSPHOLIPIDS 636 mg/4.4 mL; ALCOHOL 125 mg/4.4 mL; SODIUM OLEATE 21 mg/4.4 mL; SOYBEAN OIL 424 mg/4.4 mL; SUCROSE 238 mg/4.4 mL; WATER 2968 mg/4.4 mL

HIGHLIGHTS OF PRESCRIBING INFORMATION

These highlights do not include all the information needed to use APONVIE® safely and effectively. See full prescribing information for APONVIE.
APONVIE® (aprepitant) injectable emulsion, for intravenous use
Initial U.S. Approval: 2003

1 INDICATIONS AND USAGE

APONVIE is a substance P/neurokinin-1 (NK1) receptor antagonist, indicated for the prevention of postoperative nausea and vomiting (PONV) in adults.

Limitations of Use:

APONVIE has not been studied for treatment of established nausea and vomiting. (1)

2 DOSAGE AND ADMINISTRATION

The recommended dose is 32 mg administered as a 30 second intravenous injection prior to induction of anesthesia. (2.1)

3 DOSAGE FORMS AND STRENGTHS

Injectable emulsion: 32 mg/4.4 mL (7.2 mg/mL) in single-dose vial. (3)

4 CONTRAINDICATIONS

- Known hypersensitivity to any component of this product. (4, 5.1)
- Concurrent use with pimozide. (4)

5 WARNINGS AND PRECAUTIONS

- Hypersensitivity Reactions (including anaphylaxis): May occur during or soon after administration. If symptoms occur, administer appropriate medical therapy. (4, 5.1)
- CYP3A4 Interactions: Aprepitant is a substrate, weak-to-moderate inhibitor, and inducer of CYP3A4; see full prescribing information. (5.2, 7.2)
- Warfarin (a CYP2C9 substrate): Risk of decreased INR of prothrombin time; monitor INR in 2-week period, particularly at 7 to 10 days, following administration of APONVIE. (5.3, 7.1)
- Hormonal Contraceptives: Efficacy of contraceptives may be reduced for 28 days following administration of aprepitant. Use effective alternative or back-up methods of non-hormonal contraception. (5.4, 7.1, 8.3)

6 ADVERSE REACTIONS

Most common adverse reactions (incidence ≥3%) are (6.1):

- Single-dose APONVIE: constipation, fatigue, and headache.
- Single-dose oral aprepitant: constipation and hypotension.

To report SUSPECTED ADVERSE REACTIONS, contact Heron Therapeutics, Inc. at 1-844-437-6611 and www.APONVIE.com or FDA at 1-800-FDA-1088 or www.fda.gov/medwatch.

7 DRUG INTERACTIONS

See full prescribing information for a list of clinically significant drug interactions. (4, 5.2, 5.3, 5.4, 7.1, 7.2)

8 USE IN SPECIFIC POPULATIONS

Pregnancy: May cause fetal harm. (8.1)

FULL PRESCRIBING INFORMATION

1 INDICATIONS AND USAGE

APONVIE is indicated for the prevention of postoperative nausea and vomiting (PONV) in adults.

Limitations of Use

APONVIE has not been studied for the treatment of established nausea and vomiting.

2 DOSAGE AND ADMINISTRATION

2.1 Recommended Dosage

The recommended dose in adults of APONVIE is 32 mg administered as a 30 second intravenous injection prior to induction of anesthesia.

2.2 Preparation and Administration

- Inspect the vial for particulate matter and discoloration prior to administration; discard if present. APONVIE is opaque and off-white to amber in color.
- Aseptically withdraw 4.4 mL from the vial.
- Flush the infusion line with normal saline before and after administration of APONVIE.

2.3 Compatibilities

APONVIE is compatible with 0.9% Sodium Chloride Injection, USP or 5% Dextrose Injection, USP, and solutions containing divalent cations (e.g., calcium, magnesium), including Lactated Ringer's Solution.

3 DOSAGE FORMS AND STRENGTHS

Injectable emulsion: 32 mg/4.4 mL (7.2 mg/mL) aprepitant as an opaque, off-white to amber emulsion, in a single-dose vial.

4 CONTRAINDICATIONS

APONVIE is contraindicated in patients:

- with a history of hypersensitivity to aprepitant or any component of the product [see Description (11)]. Hypersensitivity reactions have included anaphylaxis [see Warnings and Precautions (5.1)].
- taking pimozide. Inhibition of CYP3A4 by aprepitant could result in elevated plasma concentrations of pimozide, which is a CYP3A4 substrate, potentially causing serious or life-threatening reactions, such as QT prolongation, a known adverse reaction of pimozide [see Drug Interactions (7.1)].

5 WARNINGS AND PRECAUTIONS

5.1 Hypersensitivity Reactions

Serious hypersensitivity reactions, including anaphylaxis, during or soon after administration of aprepitant have occurred. Symptoms including dyspnea, eye swelling, flushing, pruritus, and wheezing have been reported [see Adverse Reactions (6.2)].

Monitor patients during and after administration. If hypersensitivity reactions occur, administer appropriate medical therapy. Do not administer APONVIE in patients who experience these symptoms with previous use of aprepitant.

5.2 Clinically Significant CYP3A4 Drug Interactions

Aprepitant is a substrate, a weak-to-moderate (dose-dependent) inhibitor, and an inducer of CYP3A4.

- Use of pimozide, a CYP3A4 substrate, with APONVIE is contraindicated [see Contraindications (4)].
- Use of APONVIE with strong CYP3A4 inhibitors (e.g., ketoconazole) may increase plasma concentrations of aprepitant and result in an increased risk of adverse reactions related to APONVIE [see Drug Interactions (7.2)].
- Use of APONVIE with strong CYP3A4 inducers (e.g., rifampin) may result in a reduction in aprepitant plasma concentrations and decreased efficacy of APONVIE [see Drug Interactions (7.2)].

5.3 Decrease in INR with Concomitant Warfarin

Use of aprepitant with warfarin, a CYP2C9 substrate, may result in a clinically significant decrease in the International Normalized Ratio (INR) of prothrombin time [see Clinical Pharmacology (12.3)]. Monitor the INR in patients on chronic warfarin therapy in the 2-week period, particularly at 7 to 10 days, following administration of APONVIE [see Drug Interactions (7.1)].

5.4 Risk of Reduced Efficacy of Hormonal Contraceptives

The efficacy of hormonal contraceptives may be reduced for 28 days following administration of APONVIE [see Clinical Pharmacology (12.3)]. Advise patients to use effective alternative or back-up methods of non-hormonal contraception for 1 month following administration of APONVIE [see Drug Interactions (7.1) and Use in Specific Populations (8.3)].

6 ADVERSE REACTIONS

The following clinically significant adverse reactions are described elsewhere in the labeling:

- Hypersensitivity Reactions [see Warnings and Precautions (5.1)]

6.1 Clinical Trials Experience

Because clinical trials are conducted under widely varying conditions, adverse reaction rates observed in the clinical trials of a drug cannot be directly compared to rates in the clinical trials of another drug and may not reflect the rates observed in clinical practice.

The safety of APONVIE for prevention of PONV was evaluated as a single dose in healthy subjects and established from adequate and well-controlled studies of oral aprepitant [see Clinical Studies (14)]. Adverse reactions observed in these studies are described below.

Safety of APONVIE

A total of 51 healthy subjects received a single 32 mg dose of APONVIE as a 30 second intravenous injection. Adverse reactions reported in at least 3% of subjects were constipation (8%), fatigue (6%), and headache (4%).

Safety of Oral Aprepitant

In 2 active-controlled, double-blind clinical studies in patients receiving general anesthesia (Studies 1 and 2), 40 mg oral aprepitant was compared to 4 mg intravenous ondansetron [see Clinical Studies (14)].

There were 564 patients treated with oral aprepitant and 538 patients treated with ondansetron.

The most common adverse reactions reported in patients treated with oral aprepitant for PONV in pooled Studies 1 and 2 are listed in Table 1.

Table 1: Most Common Adverse Reactions in Oral Aprepitant-Treated Patients in a Pooled Analysis of PONV Studies [Reported in ≥3% of patients treated with oral aprepitant 40 mg and at a greater incidence than with ondansetron.]
 | Oral Aprepitant 40 mg (N = 564) | Ondansetron (N = 538)
Constipation | 9% | 8%
hypotension | 6% | 5%

In a pooled analysis of PONV studies, less common adverse reactions reported in more than 0.5% of patients treated with oral aprepitant and at a greater incidence than ondansetron were dizziness and urticaria.

In addition, two serious adverse reactions were reported in PONV clinical studies of oral aprepitant in patients taking a higher than recommended dose: one case of constipation, and one case of sub-ileus.

Other Studies

Angioedema, urticaria, and Stevens-Johnson syndrome were reported as serious adverse reactions in patients receiving oral aprepitant in non-PONV studies.

6.2 Postmarketing Experience

The following adverse reactions have been identified during post-approval use of aprepitant. Because these reactions are reported voluntarily from a population of uncertain size, it is not always possible to reliably estimate their frequency or establish a causal relationship to drug exposure.

Skin and subcutaneous tissue disorders: pruritus, rash, urticaria, Stevens-Johnson syndrome/toxic epidermal necrolysis [see Warnings and Precautions (5.1)].

Immune system disorders: hypersensitivity reactions including anaphylaxis and anaphylactic shock [see Contraindications (4) and Warnings and Precautions (5.1)].

Nervous system disorders: ifosfamide-induced neurotoxicity reported after aprepitant and ifosfamide coadministration.

7 DRUG INTERACTIONS

7.1 Effect of Aprepitant on the Pharmacokinetics of Other Drugs

Aprepitant is a substrate, a weak-to-moderate (dose-dependent) inhibitor, and an inducer of CYP3A4. Aprepitant is also an inducer of CYP2C9 [see Clinical Pharmacology (12.3)].

Table 2 includes drug interactions affecting drugs co-administered with APONVIE and instructions for preventing or managing them.

Table 2: Drug Interactions Affecting Drugs When Co-Administered with APONVIE
Pimozide
Clinical Impact | Increased pimozide exposure.
Intervention | APONVIE is contraindicated [see Contraindications (4)].
Hormonal Contraceptives
Clinical Impact | Decreased hormonal exposure for 28 days after administration of APONVIE [see Warnings and Precautions (5.3), Use in Specific Populations (8.3), and Clinical Pharmacology (12.3)].
Intervention | Effective alternative or back-up methods of contraception (such as condoms and spermicides) should be used for 1 month following administration of APONVIE.
Examples | birth control pills, transdermal systems, implants, and certain intrauterine systems
CYP2C9 Substrates
Warfarin
Clinical Impact | Decreased warfarin exposure and decreased prothrombin time (INR) [see Warnings and Precautions (5.2) and Clinical Pharmacology (12.3)].
Intervention | In patients on chronic warfarin therapy, monitor prothrombin time (INR) in the 2-week period, particularly at 7 to 10 days, following administration of APONVIE.
Other Antiemetic Agents
5-HT3 Antagonists
Clinical Impact | No change in the exposure of the 5-HT3 antagonist [see Clinical Pharmacology (12.3)].
Intervention | No dosage adjustment needed.
Examples | ondansetron, granisetron, dolasetron
Corticosteroids
Clinical Impact | No clinically significant change in the exposure of dexamethasone or methylprednisolone [see Clinical Pharmacology (12.3)].
Intervention | No dosage adjustment needed.

7.2 Effect of Other Drugs on the Pharmacokinetics of Aprepitant

Aprepitant is a CYP3A4 substrate [see Clinical Pharmacology (12.3)]. Table 3 includes drug interactions affecting APONVIE when co-administered with other drugs and instructions for preventing them.

Table 3: Drug Interactions Affecting APONVIE When Co-Administered with Other Drugs
Strong CYP3A4 Inhibitors
Clinical Impact | Significantly increased exposure of aprepitant may increase the risk of adverse reactions associated with APONVIE [see Clinical Pharmacology (12.3)].
Intervention | Avoid concomitant use of APONVIE.
Examples | ketoconazole, itraconazole, nefazodone, troleandomycin, clarithromycin, ritonavir, nelfinavir
Strong CYP3A4 Inducers
Clinical Impact | Substantially decreased exposure of aprepitant in patients chronically taking a strong CYP3A4 inducer may decrease the efficacy of APONVIE [see Clinical Pharmacology (12.3)].
Intervention | Avoid concomitant use of APONVIE.
Examples | rifampin, carbamazepine, phenytoin

8 USE IN SPECIFIC POPULATIONS

8.1 Pregnancy

Risk Summary

There are insufficient data on aprepitant use in pregnant women to identify a drug-associated risk of major birth defects, miscarriage or other adverse maternal or fetal outcomes. Avoid use of APONVIE in pregnant women due to the alcohol content (see Clinical Considerations). In animal reproduction studies, no adverse developmental effects were observed in rats or rabbits exposed during the period of organogenesis to systemic drug concentrations (area under the plasma-concentration time curve [AUC]) of oral aprepitant approximately 4.8 times the exposure at the recommended human dose of APONVIE (see Data).

The background risk of major birth defects and miscarriage for the indicated populations is unknown. All pregnancies have a background risk of birth defect, loss, or other adverse outcomes. In the U.S. general population, the estimated background risk of major birth defects and miscarriage in clinically recognized pregnancies is 2% to 4% and 15% to 20%, respectively.

Clinical Considerations

Fetal/Neonatal Adverse Reactions

APONVIE contains alcohol. Published studies have demonstrated that alcohol is associated with fetal harm including central nervous system abnormalities, behavioral disorders, and impaired intellectual development. There is no safe level of alcohol exposure in pregnancy; therefore, avoid use of APONVIE in pregnant women.

Data

Animal Data

In embryofetal development studies in rats and rabbits, aprepitant was administered during the period of organogenesis at oral doses up to 1000 mg/kg twice daily (rats) and up to the maximum tolerated dose of 125 mg/kg/day (rabbits). No embryofetal lethality or malformations were observed at any dose level in either species. The exposures (AUC) in pregnant rats at 1000 mg/kg twice daily and in pregnant rabbits at 125 mg/kg/day were approximately 4.8 times the exposure at the recommended human dose of APONVIE. Aprepitant crosses the placenta in rats and rabbits.

8.2 Lactation

Risk Summary

There are no data on the presence of aprepitant in human milk, the effects on the breastfed infant, or the effects on milk production. Aprepitant is present in rat milk. When a drug is present in animal milk, it is likely that the drug will be present in human milk. The developmental and health benefits of breastfeeding should be considered along with the mother's clinical need for APONVIE and any potential adverse effects on the breastfed infant from APONVIE or from the underlying maternal condition.

8.3 Females and Males of Reproductive Potential

Contraception

Upon administration of APONVIE, the efficacy of hormonal contraceptives may be reduced. Advise females of reproductive potential using hormonal contraceptives to use an effective alternative or back-up non-hormonal contraceptive (such as condoms or spermicides) for 1 month following administration of APONVIE [see Warnings and Precautions (5.4), Drug Interactions (7.1), and Clinical Pharmacology (12.3)].

8.4 Pediatric Use

The safety and effectiveness of APONVIE have not been established in pediatric patients.

Juvenile Animal Study

A study was conducted in young rats to evaluate the effects of aprepitant on growth and on neurobehavioral and sexual development. Rats were treated at oral doses up to the maximum feasible dose of 1000 mg/kg twice daily from the early postnatal period (Postnatal Day 10) through Postnatal Day 58. Slight changes in the onset of sexual maturation were observed in female and male rats; however, there were no effects on mating, fertility, embryonic-fetal survival, or histomorphology of the reproductive organs. There were no effects in neurobehavioral tests of sensory function, motor function, and learning and memory.

8.5 Geriatric Use

Of the 1120 adult patients treated with oral aprepitant in PONV clinical studies, 7% were aged 65 and over, while 2% were aged 75 and over. Clinical studies of aprepitant did not include sufficient numbers of subjects aged 65 and over to determine whether they responded differently from younger subjects. Other reported clinical experience has not identified differences in responses between the elderly and younger patients. No clinically meaningful differences in the pharmacokinetics of oral aprepitant were observed in healthy geriatric subjects compared to younger adult subjects [see Clinical Pharmacology (12.3)].

10 OVERDOSAGE

Headache, fatigue, and dizziness were reported in healthy subjects receiving a single dose of 100 or 130 mg aprepitant injectable emulsion (3.1 to 4 times the recommended dose).

Drowsiness and headache were reported in one patient who ingested 1440 mg of oral aprepitant.

In the event of overdose, general supportive treatment and monitoring should be provided.

Aprepitant is not removed by hemodialysis.

11 DESCRIPTION

APONVIE injectable emulsion contains the active ingredient, aprepitant. Aprepitant is a substance P/neurokinin 1 (NK1) receptor antagonist, an antiemetic agent, and chemically described as 5-[[(2R,3S)-2-[(1R)-1-[3,5bis(trifluoromethyl)phenyl]ethoxy]-3-(4-fluorophenyl)-4-morpholinyl]methyl]-1,2-dihydro-3H-1,2,4-triazol-3-one.

Its empirical formula is C23H21F7N4O3, and its structural formula is:

Aprepitant is a white to off-white crystalline solid, with a molecular weight of 534.43. It is practically insoluble in water. Aprepitant is sparingly soluble in ethanol and isopropyl acetate and slightly soluble in acetonitrile.

APONVIE (aprepitant) injectable emulsion is a sterile, opaque, off-white to amber liquid in a single-dose vial for intravenous use. Each vial contains 32 mg aprepitant in 4.4 mL of emulsion. The emulsion also contains the following inactive ingredients: dehydrated alcohol (125 mg), egg lecithin (636 mg), sodium oleate (21 mg), soybean oil (424 mg), sucrose (238 mg), and water for injection (2968 mg).

12 CLINICAL PHARMACOLOGY

12.1 Mechanism of Action

Aprepitant is a selective high-affinity antagonist of human substance P/neurokinin 1 (NK1) receptors. Aprepitant has little or no affinity for serotonin (5-HT3), dopamine, and corticosteroid receptors, the targets of existing therapies for postoperative nausea and vomiting (PONV). Aprepitant has been shown in animal models to inhibit emesis via central actions. Animal and human Positron Emission Tomography (PET) studies with aprepitant have shown that it crosses the blood brain barrier and occupies brain NK1 receptors.

12.2 Pharmacodynamics

NK1 Receptor Occupancy

In two single-blind, multiple-dose, randomized, and placebo-controlled studies, healthy young men received oral aprepitant doses of 10 mg (N=2), 30 mg (N=3), 100 mg (N=3), or 300 mg (N=5) once daily (0.08, 0.24, 0.8, and 2.4 times a single 125 mg dose of oral aprepitant, respectively) for 14 days with 2 or 3 subjects on placebo. Both plasma aprepitant concentration and NK1 receptor occupancy in the corpus striatum by PET were evaluated, at predose and 24 hours after the last dose. At aprepitant plasma concentrations of approximately 10 ng/mL and 100 ng/mL, the NK1 receptor occupancies were approximately 50% and 90%, respectively. The oral aprepitant regimen produced mean trough plasma aprepitant concentrations greater than 500 ng/mL in adults, which would be expected to, based on the fitted curve with the Hill equation, result in greater than 95% brain NK1 receptor occupancy. However, the receptor occupancy for the PONV dosing regimen has not been determined. In addition, the relationship between NK1 receptor occupancy and the clinical efficacy of aprepitant has not been established.

Cardiac Electrophysiology

In a randomized, double-blind, positive-controlled, thorough QTc study, a single 200 mg intravenous dose of fosaprepitant, a prodrug of aprepitant, had no effect on the QTc interval. QT prolongation with the recommended APONVIE dosing regimen is not expected.

12.3 Pharmacokinetics

Absorption

Following administration of a single intravenous 32 mg dose of APONVIE administered as a 30 second injection to healthy subjects, mean (CV%) area under the plasma concentration-time curve (AUC0-∞) was 7.8 (27.4%) mcg∙hr/mL and mean plasma concentration at 5 minutes post-dose was 2.1 (19%) mcg/mL.

In healthy subjects, a single dose of 32 mg of APONVIE administered as a 30 second intravenous injection resulted in a 13% higher AUC0-∞ of aprepitant compared to a single oral dose of 40 mg aprepitant, which was not considered clinically meaningful.

Distribution

Aprepitant was greater than 99% bound to plasma proteins. The mean volume of distribution following APONVIE administration was approximately 72 L in healthy subjects.

Aprepitant crossed the blood-brain barrier in humans [see Clinical Pharmacology (12.1)].

Elimination

Metabolism

Aprepitant underwent extensive metabolism. In vitro studies using human liver microsomes indicated that aprepitant was metabolized primarily by CYP3A4 with minor metabolism by CYP1A2 and CYP2C19. Metabolism was largely via oxidation at the morpholine ring and its side chains. No metabolism by CYP2D6, CYP2C9, or CYP2E1 was detected.

In healthy young adults, aprepitant accounted for approximately 24% of the radioactivity in plasma over 72 hours following a single oral 300 mg dose of [^14C]-aprepitant, indicating a substantial presence of metabolites in the plasma. Seven metabolites of aprepitant, which were only weakly active, had been identified in human plasma.

Excretion

Aprepitant was eliminated primarily by metabolism; aprepitant was not renally excreted. The mean terminal half-life of aprepitant following administration of APONIVE was 12 hours. The mean plasma clearance of aprepitant was 4.4 L/h.

Specific Populations

Geriatric Patients

Following oral administration of a single 125 mg dose of aprepitant on Day 1 and 80 mg once daily on Days 2 through 5, the AUC0-24hr of aprepitant was 21% higher on Day 1 and 36% higher on Day 5 in healthy elderly subjects (65 years and older) relative to younger adult subject. The Cmax was 10% higher on Day 1 and 24% higher on Day 5 in healthy elderly subjects relative to younger adult subjects. These differences are not considered clinically meaningful [see Use in Specific Populations (8.5)].

Male and Female Patients

Following oral administration of a single dose of aprepitant ranging from 40 mg to 375 mg, the AUC0-24hr and Cmax are 9% and 17% higher in females as compared with males. The half-life of aprepitant was approximately 25% lower in females as compared with males. These differences are not considered clinically meaningful.

Racial or Ethnic Groups

Following oral administration of a single dose of aprepitant, ranging from 40 mg to 375 mg, the AUC0-24hr and Cmax were approximately 27% and 19% higher in Hispanics as compared with Caucasians. The AUC0-24hr and Cmax were 74% and 47% higher in Asians as compared to Caucasians. There was no difference in AUC0-24hr or Cmax between Caucasians and Blacks. These differences are not considered clinically meaningful.

Patients with Renal Impairment

A single 240 mg oral dose of aprepitant was administered to patients with severe renal impairment (creatinine clearance less than 30 mL/min/1.73 m^2 as measured by 24-hour urinary creatinine clearance) and to patients with end stage renal disease (ESRD) requiring hemodialysis. In patients with severe renal impairment, the AUC0-∞ of total aprepitant (unbound and protein bound) decreased by 21% and Cmax decreased by 32%, relative to healthy subjects (creatinine clearance greater than 80 mL/min estimated by Cockcroft-Gault method). In patients with ESRD undergoing hemodialysis, the AUC0-∞ of total aprepitant decreased by 42% and Cmax decreased by 32%. Due to modest decreases in protein binding of aprepitant in patients with renal disease, the AUC of pharmacologically active unbound drug was not significantly affected in patients with renal impairment compared with healthy subjects. Hemodialysis conducted 4 or 48 hours after dosing had no significant effect on the pharmacokinetics of aprepitant; less than 0.2% of the dose was recovered in the dialysate.

No clinically meaningful changes in the pharmacokinetics of aprepitant are expected in patients with any degree of renal impairment following administration of a single dose of APONVIE 32 mg as an intravenous injection.

Patients with Hepatic Impairment

Following administration of a single 125 mg oral dose of aprepitant on Day 1 and 80 mg once daily on Days 2 and 3 to patients with mild hepatic impairment (Child-Pugh score 5 to 6), the AUC0-24hr of aprepitant was 11% lower on Day 1 and 36% lower on Day 3, as compared with healthy subjects given the same regimen. In patients with moderate hepatic impairment (Child Pugh score 7 to 9), the AUC0-24hr of aprepitant was 10% higher on Day 1 and 18% higher on Day 3, as compared with healthy subjects given the same regimen. These differences in AUC0-24hr are not considered clinically meaningful.

No clinically meaningful changes in the pharmacokinetics of aprepitant are expected in patients with mild or moderate hepatic impairment following administration of a single dose of APONVIE 32 mg as an intravenous injection. There are no clinical or pharmacokinetic data in patients with severe hepatic impairment (Child-Pugh score greater than 9).

Body Mass Index (BMI)

For every 5 kg/m^2 increase in BMI, AUC0-24hr and Cmax of aprepitant decrease by 9% and 10%. BMI of subjects in the analysis ranged from 18 kg/m^2 to 36 kg/m^2. This change is not considered clinically meaningful.

Drug Interactions Studies

Aprepitant is a substrate, a weak-to-moderate (dose-dependent) inhibitor, and an inducer of CYP3A4. Aprepitant is also an inducer of CYP2C9. Aprepitant is unlikely to interact with drugs that are substrates for the P-glycoprotein transporter.

Aprepitant acts as a weak inhibitor of CYP3A4 when administered as a single intravenous 32 mg dose of APONVIE.

Effects of Aprepitant on the Pharmacokinetics of Other Drugs

CYP3A4 Substrates:

Midazolam: Oral aprepitant 40 mg administered as a single oral dose on Day 1 increased the AUC of oral midazolam 2 mg by approximately 1.2-fold on Day 1. This effect was not considered clinically meaningful.

Corticosteroids:

Dexamethasone: A single dose of oral aprepitant 40 mg when coadministered with a single dose of dexamethasone 20 mg, increased the AUC of dexamethasone by 1.45-fold, which is not considered clinically meaningful.

Methylprednisolone: Although the concomitant administration of methylprednisolone with the single 40 mg dose of oral aprepitant has not been studied, a single 40 mg dose of oral aprepitant produces a weak inhibition of CYP3A4 (based on midazolam interaction study) and it is not expected to alter the plasma concentrations of methylprednisolone to a clinically meaningful degree.

CYP2C9 substrates:

Warfarin: A single 125 mg dose of oral aprepitant was administered on Day 1 and 80 mg/day on Days 2 and 3 to subjects who were stabilized on chronic warfarin therapy. Although there was no effect of oral aprepitant on the plasma AUC of R(+) or S(-) warfarin determined on Day 3, there was a 34% decrease in S(-) warfarin trough concentration accompanied by a 14% decrease in the prothrombin time (reported as International Normalized Ratio or INR) 5 days after completion of dosing with oral aprepitant [see Drug Interactions (7.1)].

Tolbutamide: Oral aprepitant, when given as a 40 mg single dose on Day 1, decreased the AUC of tolbutamide by 8% on Day 2, 16% on Day 4, 15% on Day 8, and 10% on Day 15, when a single dose of tolbutamide 500 mg was administered prior to the administration of oral aprepitant 40 mg and on Days 2, 4, 8, and 15. This effect was not considered clinically meaningful.

Other Drugs:

Oral contraceptives: When a daily dosage of an oral contraceptive containing ethinyl estradiol and norgestimate was administered on Days 1 through 21, and oral aprepitant 40 mg was given on Day 8, the AUC of ethinyl estradiol decreased by 4% and by 29% on Day 8 and Day 12, respectively, while the AUC of norelgestromin increased by 18% on Day 8 and decreased by 10% on Day 12. In addition, the trough concentrations of ethinyl estradiol and norelgestromin on Days 8 through 21 were generally lower following coadministration of the oral contraceptive with oral aprepitant 40 mg on Day 8 compared to the trough levels following administration of the oral contraceptive alone [see Drug Interactions (7.1)].

P-glycoprotein substrates: Aprepitant is unlikely to interact with drugs that are substrates for the P-glycoprotein transporter, as demonstrated by the lack of interaction of oral aprepitant with digoxin in a clinical drug interaction study.

5-HT3 antagonists: In clinical drug interaction studies, aprepitant did not have clinically important effects on the pharmacokinetics of ondansetron, granisetron, or hydrodolasetron (the active metabolite of dolasetron).

Effect of Other Drugs on the Pharmacokinetics of Aprepitant

Rifampin: When a single 375 mg dose of oral aprepitant was administered on Day 9 of a 14-day regimen of 600 mg/day of rifampin, a strong CYP3A4 inducer, the AUC of aprepitant decreased approximately 11-fold and the mean terminal half-life decreased approximately 3-fold [see Drug Interactions (7.2)].

Ketoconazole: When a single 125 mg dose of oral aprepitant was administered on Day 5 of a 10-day regimen of 400 mg/day of ketoconazole, a strong CYP3A4 inhibitor, the AUC of aprepitant increased approximately 5-fold and the mean terminal half-life of aprepitant increased approximately 3-fold [see Drug Interactions (7.2)].

Diltiazem: In a study in 10 subjects with mild to moderate hypertension, administration of 100 mg of fosaprepitant, a prodrug of aprepitant, as an intravenous infusion with 120 mg of diltiazem, a moderate CYP3A4 inhibitor administered three times daily, resulted in a 1.5-fold increase in the aprepitant AUC and a 1.4-fold increase in the diltiazem AUC. This effect was not considered clinically meaningful.

When fosaprepitant was administered with diltiazem, the mean maximum decrease in diastolic blood pressure was greater than that observed with diltiazem alone (24.3 ± 10.2 mm Hg with fosaprepitant versus 15.6 ± 4.1 mm Hg without fosaprepitant). The mean maximum decrease in systolic blood pressure was also greater after co-administration of diltiazem with fosaprepitant than administration of diltiazem alone (29.5 ± 7.9 mm Hg with fosaprepitant versus 23.8 ± 4.8 mm Hg without fosaprepitant). Co-administration of fosaprepitant and diltiazem, however, did not result in any additional clinically meaningful changes in heart rate or PR interval, beyond those changes observed with diltiazem alone.

Paroxetine: Coadministration of once daily doses of oral aprepitant 85 mg or 170 mg, with paroxetine 20 mg once daily, resulted in a decrease in AUC by approximately 25% and Cmax by approximately 20% of both aprepitant and paroxetine. This effect was not considered clinically meaningful.

13 NONCLINICAL TOXICOLOGY

13.1 Carcinogenesis, Mutagenesis, Impairment of Fertility

Carcinogenesis

Carcinogenicity studies were conducted in Sprague-Dawley rats and in CD-1 mice for 2 years. In the rat carcinogenicity studies, animals were treated with oral doses ranging from 0.05 to 1000 mg/kg twice daily. The highest dose produced systemic exposures to aprepitant (AUC) approximately 5.1 times the human exposure from APONVIE 32 mg. Treatment with aprepitant at doses of 5 to 1000 mg/kg twice daily caused an increase in the incidences of thyroid follicular cell adenomas and carcinomas in male rats. In female rats, it produced hepatocellular adenomas at 5 to 1000 mg/kg twice daily and hepatocellular carcinomas and thyroid follicular cell adenomas at 125 to 1000 mg/kg twice daily. In the mouse carcinogenicity studies, the animals were treated with oral doses ranging from 2.5 to 2000 mg/kg/day. The highest dose produced a systemic exposure approximately 11.5 times the human exposure at the recommended human dose of APONVIE. Treatment with aprepitant produced skin fibrosarcomas at 125 and 500 mg/kg/day doses in male mice.

Mutagenesis

Aprepitant was not genotoxic in the Ames test, the human lymphoblastoid cell (TK6) mutagenesis test, the rat hepatocyte DNA strand break test, the Chinese hamster ovary (CHO) cell chromosome aberration test, and the mouse micronucleus test.

Impairment of Fertility

Oral aprepitant did not affect the fertility or general reproductive performance of male or female rats at doses up to the maximum feasible dose of 1000 mg/kg twice daily (providing exposure in male and female rats higher than the exposure at the recommended human dose of APONVIE).

14 CLINICAL STUDIES

The safety and efficacy of APONVIE have been established based on adequate and well-controlled studies of a single-dose of oral aprepitant in adults. Below is a description of the results of these adequate and well-controlled studies of oral aprepitant for the prevention of PONV.

In two multicenter, randomized, double-blind, active comparator-controlled, parallel-group clinical studies (Studies 1 and 2), oral aprepitant was compared with ondansetron for the prevention of postoperative nausea and vomiting in 1658 patients undergoing open abdominal surgery. These two studies were of similar design; however, they differed in terms of study hypothesis, efficacy analyses, and geographic location. Study 1 was a multinational study including the U.S., whereas, Study 2 was conducted entirely in the U.S.

In the two studies, patients were randomized to receive 40 mg oral aprepitant, 125 mg oral aprepitant, or 4 mg intravenous ondansetron as a single dose. Aprepitant was given orally with 50 mL of water 1 to 3 hours before anesthesia. Ondansetron was given intravenously immediately before induction of anesthesia. A comparison between the oral aprepitant 125 mg dose did not demonstrate any additional clinical benefit over the oral 40 mg dose.

Of the 564 patients who received 40 mg oral aprepitant, 92% were women and 8% were men; of these, 58% were White, 13% Hispanic American, 7% Multi-Racial, 14% Black, 6% Asian, and 2% Other. The age of patients treated with 40 mg oral aprepitant ranged from 19 to 84 years, with a mean age of 46.1 years. 46 patients were 65 years or older, with 13 patients being 75 years or older.

The antiemetic activity of oral aprepitant was evaluated during the 0 to 48 hour period following the end of surgery.

Efficacy measures in Study 1 included:

- no emesis (defined as no emetic episodes regardless of use of rescue therapy) in the 0 to 24 hours following the end of surgery (primary)
- complete response (defined as no emetic episodes and no use of rescue therapy) in the 0 to 24 hours following the end of surgery (primary)
- no emesis (defined as no emetic episodes regardless of use of rescue therapy) in the 0 to 48 hours following the end of surgery (secondary)
- time to first use of rescue medication in the 0 to 24 hours following the end of surgery (exploratory)
- time to first emesis in the 0 to 48 hours following the end of surgery (exploratory)

A closed testing procedure was applied to control the type I error for the primary endpoints.

The results of the primary and secondary endpoints for 40 mg oral aprepitant and 4 mg ondansetron are described in Table 4.

Table 4: Response Rates for Select Efficacy Endpoints (Modified-Intention-to-Treat Population) – Study 1
Treatment | n/N (%) | Oral Aprepitant vs. Ondansetron
Treatment | n/N (%) | Difference [Difference (%): oral aprepitant 40 mg minus ondansetron.] | Odds Ratio [Estimated odds ratio for oral aprepitant versus ondansetron. A value of >1 favors aprepitant over ondansetron.] | Analysis
PRIMARY ENDPOINTS
No Vomiting 0 to 24 hours (Superiority)
(no emetic episodes)
Oral aprepitant 40 mg | 246/293 (84.0) | 12.6% | 2.1 | P<0.001 [P-value of two-sided test <0.05.]
Ondansetron | 200/280 (71.4)
Complete Response (Non-inferiority: If LB [LB = lower bound of 1-sided 97.5% confidence interval for the odds ratio.] >0.65)
(no emesis and no rescue therapy, 0 to 24 hours)
Oral aprepitant 40 mg | 187/293 (63.8) | 8.8% | 1.4 | LB=1.02
Ondansetron | 154/280 (55.0)
Complete Response (Superiority: If LB >1.0)
(no emesis and no rescue therapy, 0 to 24 hours)
Oral aprepitant 40 mg | 187/293 (63.8) | 8.8% | 1.4 | LB=1.02
Ondansetron | 154/280 (55.0)
SECONDARY ENDPOINT
No Vomiting 0 to 48 hours (Superiority) (no emetic episodes)
Oral aprepitant 40 mg | 238/292 (81.5) | 15.2% | 2.3 | P<0.001 [Based on the prespecified fixed sequence multiplicity strategy, oral aprepitant 40 mg was not superior to ondansetron.]
Ondansetron | 185/279 (66.3)
n/N = Number of responders/number of patients in analysis.

In Study 1, the use of oral aprepitant did not affect the time to first use of rescue medication when compared to ondansetron. However, compared to the ondansetron group, use of oral aprepitant delayed the time to first vomiting, as depicted in Figure 1.

Figure 1: Percent of Patients Who Remain Emesis Free During the 48 Hours Following End of Surgery in Study 1

Efficacy measures in Study 2 included:

- complete response (defined as no emetic episodes and no use of rescue therapy) in the 0 to 24 hours following the end of surgery (primary)
- no emesis (defined as no emetic episodes regardless of use of rescue therapy) in the 0 to 24 hours following the end of surgery (secondary)
- no use of rescue therapy in the 0 to 24 hours following the end of surgery (secondary)
- no emesis (defined as no emetic episodes regardless of use of rescue therapy) in the 0 to 48 hours following the end of surgery (secondary)

Study 2 failed to satisfy its primary hypothesis that oral aprepitant is superior to ondansetron in the prevention of PONV as measured by the proportion of patients with complete response in the 24 hours following end of surgery.

The study demonstrated that 40 mg oral aprepitant had a clinically meaningful effect with respect to the secondary endpoint "no vomiting" during the first 24 hours after surgery and was associated with a 16% improvement over ondansetron for the no vomiting endpoint (Table 5).

Table 5: Response Rates for Select Efficacy Endpoints (Modified-Intention-to-Treat Population) – Study 2
Treatment | n/N (%) | Oral Aprepitant vs. Ondansetron
Treatment | n/N (%) | Difference [Difference (%): oral aprepitant 40 mg minus ondansetron.] | Odds Ratio [Estimated odds ratio: oral aprepitant 40 mg versus ondansetron.] | Analysis
PRIMARY ENDPOINT
Complete Response
(no emesis and no rescue therapy, 0 to 24 hours)
Oral aprepitant 40 mg | 111/248 (44.8) | 2.5% | 1.1 | 0.61
Ondansetron | 104/246 (42.3)
SECONDARY ENDPOINTS
No Vomiting
(no emetic episodes, 0 to 24 hours)
Oral aprepitant 40 mg | 223/248 (89.9) | 16.3% | 3.2 | <0.001 [Not statistically significant after prespecified multiplicity adjustment.]
Ondansetron | 181/246 (73.6)
No Use of Rescue Medication
(for established emesis or nausea, 0 to 24 hours)
Oral aprepitant 40 mg | 112/248 (45.2) | -0.7% | 1.0 | 0.83
Ondansetron | 113/246 (45.9)
No Vomiting 0 to 48 hours (Superiority)
(no emetic episodes, 0 to 48 hours)
Oral aprepitant 40 mg | 209/247 (84.6) | 17.7% | 2.7 | <0.001
Ondansetron | 164/245 (66.9)
n/N = Number of responders/number of patients in analysis.

16 HOW SUPPLIED/STORAGE AND HANDLING

APONVIE injectable emulsion is supplied as an opaque, off-white to amber emulsion in a single-dose glass vial containing 32 mg/4.4 mL (7.2 mg/mL) aprepitant:

NDC 47426-401-10 | 10 single-dose vials (NDC 47426-401-01) per carton

Storage

Refrigerate APONVIE at 2°C to 8°C (36°F to 46°F).

APONVIE can remain at room temperature 20°C to 25°C (68°F to 77°F) up to 60 days.

Do not freeze.

17 PATIENT COUNSELING INFORMATION

Hypersensitivity

Advise patients that hypersensitivity reactions, including anaphylaxis, have been reported with aprepitant [see Warnings and Precautions (5.1)]. Advise patients to seek immediate medical attention if they experience signs or symptoms of a hypersensitivity reaction, such as hives, rash and itching, skin peeling or sores, or difficulty in breathing or swallowing, or dizziness, rapid or weak heartbeat or feeling faint.

Drug Interactions

Advise patients to discuss all medications they are taking, including other prescription, non- prescription medication or herbal products [see Contraindications (4) and Warnings and Precautions (5.2)].

Warfarin: Instruct patients on chronic warfarin therapy to follow instructions from their healthcare provider regarding blood draws to monitor their INR during the 2-week period, particularly at 7 to 10 days, following administration of APONVIE [see Warnings and Precautions (5.3)].

Hormonal Contraceptives: Advise patients that administration of APONVIE may reduce the efficacy of hormonal contraceptives. Instruct patients to use effective alternative or back-up methods of non-hormonal contraception (such as condoms or spermicides) for 1 month following administration of APONVIE [see Warnings and Precautions (5.4) and Use in Specific Populations (8.3)].

Pregnancy

Advise pregnant women of the potential risk to a fetus and to avoid use of APONVIE during pregnancy [see Use in Specific Populations (8.1)].

Manufactured for: Heron Therapeutics, Inc., San Diego, CA, 92121, USA

Patent: https://www.herontx.com/patents/

APONVIE® is a registered trademark of Heron Therapeutics, Inc.

Copyright © 2022-2024 Heron Therapeutics, Inc.

All rights reserved.

PRINCIPAL DISPLAY PANEL - 10 Vial Carton

NDC 47426-401-10

How Supplied:
APONVIE injectable emulsion
is supplied in a carton
containing 10 sterile,
single-dose glass vials of
32 mg aprepitant per 4.4 mL for
intravenous administration.

Recommended Dosage:
See Prescribing Information.

APONVIE®
(aprepitant) injectible emulsion

32 mg per 4.4 mL
(7.2 mg/mL)

For Intravenous Use Only

10 x 5 mL single-dose vials -
Discard unused portion
of vial.

Storage:
Must be refrigerated,
2°C to 8°C (36°F to 46°F).
Do not freeze.

Rx Only